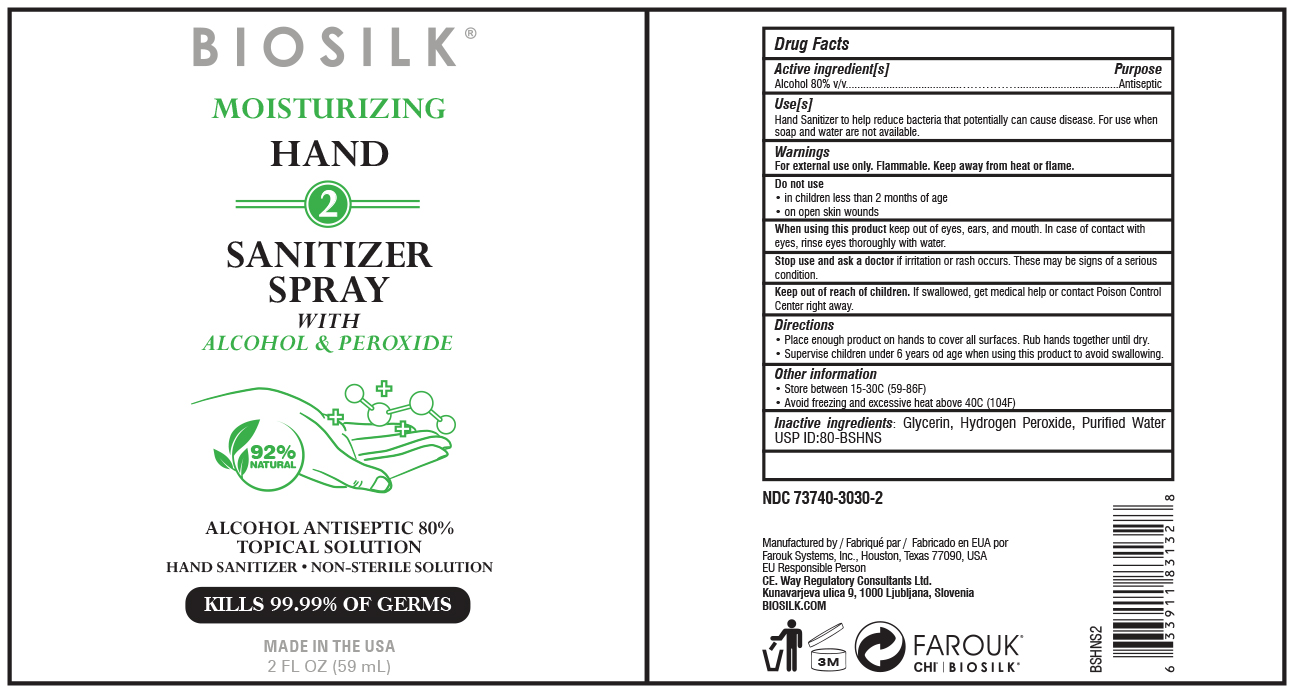 DRUG LABEL: BioSilk
NDC: 73740-3030 | Form: SPRAY
Manufacturer: Farouk Systems, Inc.
Category: otc | Type: HUMAN OTC DRUG LABEL
Date: 20200428

ACTIVE INGREDIENTS: ALCOHOL 80 g/100 g
INACTIVE INGREDIENTS: WATER 18.425 g/100 g; HYDROGEN PEROXIDE 0.125 g/100 g; GLYCERIN 1.45 g/100 g

BioSilk Hand Sanitizer Spray

Dosage & Administration

Directions
• Place enough product on hands to cover all surfaces. Rub hands together until dry.
• Supervise children under 6 years od age when using this product to avoid swallowing.

Inactive Ingredients

Inactive ingredients: Glycerin, Hydrogen Peroxide, Purified Water
USP ID:80-BSHNS

Active Ingredient

Active ingredient[s] Purpose
Alcohol 80% v/v.......................................……………...................................Antiseptic

Keep out of reach of children. If swallowed, get medical help or contact Poison Control
Center right away.

Purpose

Active ingredient[s] Purpose
Alcohol 80% v/v.......................................……………...................................Antiseptic

Use[s]
Hand Sanitizer to help reduce bacteria that potentially can cause disease. For use when
soap and water are not available.

Storage and Handling

Other information
• Store between 15-30C (59-86F)
• Avoid freezing and excessive heat above 40C (104F)

Warnings

For external use only. Flammable. Keep away from heat or flame.

Do not use
• in children less than 2 months of age
• on open skin wounds

When using this product keep out of eyes, ears, and mouth. In case of contact with
eyes, rinse eyes thoroughly with water.

Stop use and ask a doctor if irritation or rash occurs. These may be signs of a serious
condition.

Keep out of reach of children. If swallowed, get medical help or contact Poison Control
Center right away.

Indications & Usage

Active ingredient[s] Purpose
Alcohol 80% v/v.......................................……………...................................Antiseptic

Use[s]
Hand Sanitizer to help reduce bacteria that potentially can cause disease. For use when
soap and water are not available.

Principal Display Panel

BioSilk

MOISTURIZING
HAND
2
SANITIZER
SPRAY
WITH
ALCOHOL & PEROXIDE
ALCOHOL ANTISEPTIC 80%
TOPICAL SOLUTION
HAND SANITIZER • NON-STERILE SOLUTION
KILLS 99.99% OF GERMS
92%
MADE IN THE USA
2 FL OZ (59 mL)